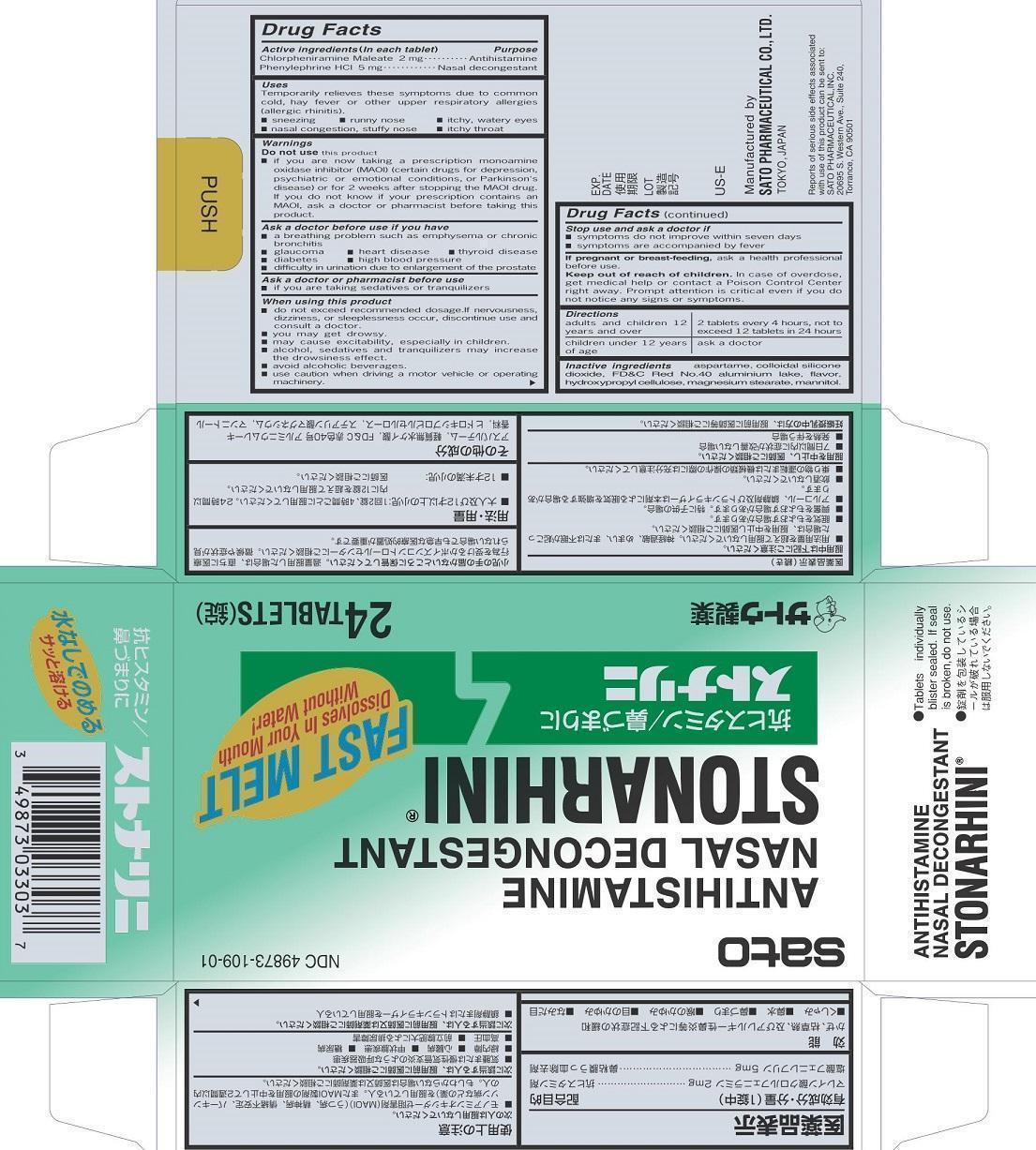 DRUG LABEL: Stonarhini
NDC: 49873-109 | Form: TABLET
Manufacturer: Sato Pharmaceutical Co., Ltd.
Category: otc | Type: HUMAN OTC DRUG LABEL
Date: 20250109

ACTIVE INGREDIENTS: CHLORPHENIRAMINE MALEATE 2 mg/1 1; PHENYLEPHRINE HYDROCHLORIDE 5 mg/1 1
INACTIVE INGREDIENTS: ASPARTAME; SILICON DIOXIDE; FD&C RED NO. 40; HYDROXYPROPYL CELLULOSE (TYPE EL); MAGNESIUM STEARATE; MANNITOL; ALUMINUM OXIDE

Stonarhini

Active ingredients (In each tablet)
Chlorpheniramine Maleate 2 mg
Phenylephrine HCl 5 mg

Purpose
Chlorpheniramine Maleate Antihistamine
Phenylephrine HCl Nasal decongestant

Uses
Temporarily relieves these symptoms due to common cold, hay fever or other upper respiratory allergies (allergic rhinitis).
■ sneezing ■ runny nose ■ itchy, watery eyes
■ nasal congestion, stuffy nose ■ itchy throat

Warnings

Enter section text here

Do not use this product
■ if you are now taking a prescription monoamine oxidase inhibitor (MAOI) (certain drugs for depression, psychiatric or emotional conditions, or Parkinson’s disease) or for 2 weeks after stopping the MAOI drug. If you do not know if your prescription contains an MAOI, ask a doctor or pharmacist before taking this priduct.

Ask a doctor before use if you have
■ a breathing problem such as emphysema or chronic bronchitis
■ glaucoma ■ heart disease ■ thyroid disease
■ diabetes ■ high blood pressure
■difficulty in urination due to enlargement of the prostate

Ask a doctor or pharmacist before use
■ if you are taking sedatives or tranquilizers

When using this product
■ do not exceed recommended dosage. If nervousness, dizziness, or sleeplessness occur, discontinue use and consult a doctor.
■ you may get drowsy.
■ may cause excitability, especially in children.
■ alcohol, sedatives and tranquilizers may increase the drowsiness effect.
■ avoid alcoholic beverages.
■ use caution when driving a motor vehicle or operating machinery.

Stop use and ask a doctor if
■ symptoms do not improve within seven days
■ symptoms are accompanied by fever

PREGNANCY OR BREAST FEEDING

If pregnant or breast-feeding, ask a health professional before use.

Keep out of reach of children. In case of overdose, get medical help or contact a Poison Control Center right away. Prompt attention is critical even if you do not notice any signs or symptoms.

Directions
adults and children 12 years and over: 2 tablets every 4 hours, not to exceed 12 tablets in 24 hours
children under 12 years of age: ask a doctor

INACTIVE INGREDIENT

Inactive ingredients aspartame, colloidal silicone dioxide, FD&C Red No. 40 aluminum Lake, flavor, hydroxypropyl cellulose, magnesium stearate, mannitol.